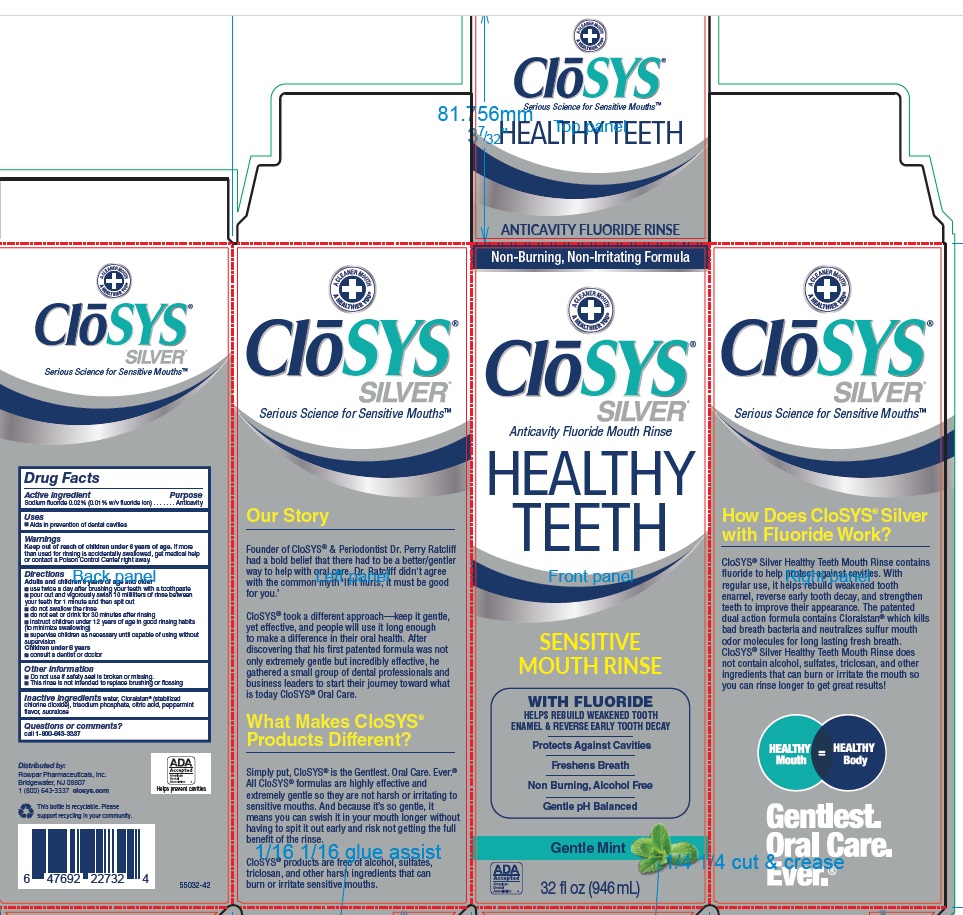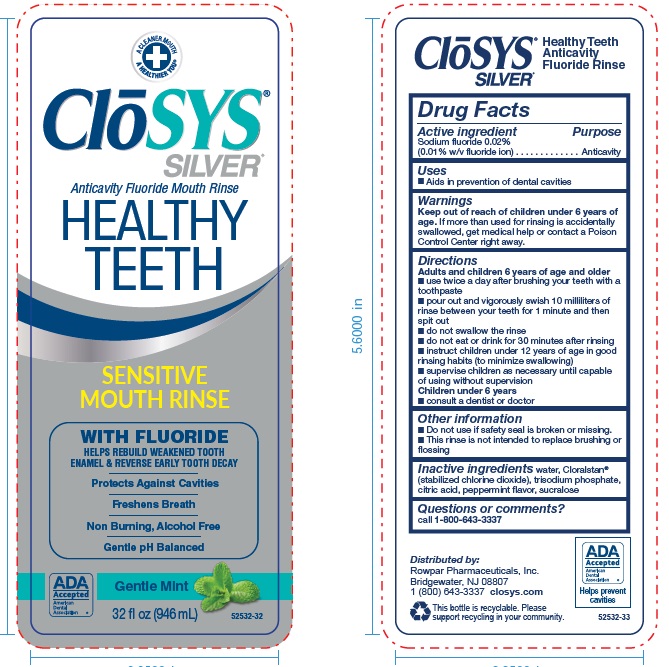 DRUG LABEL: CloSYS Silver Sensitive Mouth Rinse
NDC: 58578-0517 | Form: RINSE
Manufacturer: Rowpar Pharmaceuticals, Inc.
Category: otc | Type: HUMAN OTC DRUG LABEL
Date: 20250516

ACTIVE INGREDIENTS: SODIUM FLUORIDE 0.02 g/100 mL
INACTIVE INGREDIENTS: WATER; CHLORINE DIOXIDE; SODIUM PHOSPHATE, TRIBASIC, DODECAHYDRATE; ANHYDROUS CITRIC ACID; PEPPERMINT; SUCRALOSE

ClōSYS® Silver® Anticavity Fluoride Rinse

Active ingredient

Sodium fluoride 0.02% (0.01% w/v fluoride ion)

Purpose

Anticavity

Uses

▪ Aids in the prevention of dental cavities

Keep out of reach of children under 6 years of age. If more than used for rinsing is accidentally swallowed, get medical help or contact a Poison Control Center right away.

Directions

Adults and children 6 years of age and older

- use twice a day after brushing your teeth with a toothpaste
- pour out and vigorously swish 10 milliliters of rinse between your teeth for 1 minute and then spit out
- do not swallow the rinse
- do not eat or drink for 30 minutes after rinsing
- instruct children under 12 years of age in good rinsing habits (to minimize swallowing)
- supervise children as necessary until capable of using without supervision

Children under 6 years

- consult a dentist or doctor

Other Information

- Do not use if safety seal is broken or missing.
- This rinse is not intended to replace brushing or flossing

Inactive ingredients

water, Cloralstan® (stabilized chlorine dioxide), trisodium phosphate, citric acid, peppermint flavor, sucralose

Questions or comments?
Call 1-800-643-3337

PACKAGE LABEL.PRINCIPAL DISPLAY PANEL

ClōSYS®
SILVER®
Anticavity Fluoride Mouth Rinse
HEALTHY TEETH
SENSITIVE MOUTH RINSE
WITH FLUORIDE
HELPS REBUILD WEAKENED TOOTH
ENAMEL & REVERSE EARLY TOOTH DECAY
Protects Against Cavities
Freshens Breath
Non Burning, Alcohol Free
Gentle pH Balanced
Gentle Mint
32 fl oz (946 mL) 52532-32
Distributed by:
Rowpar Pharmaceuticals, Inc.
Bridgewater, NJ 08807
1 (800) 643-3337 closys.com
This bottle is recyclable. Please
support recycling in your community 52532-33

Non-Burning, Non-Irritating Formula
A CLEANER MOUTH
A HEALTHIER YOU®
ClōSYS®
SILVER®
Anticavity Fluoride Mouth Rinse
HEALTHY
TEETH
SENSITIVE
MOUTH RINCE
WITH FLUORIDE
HELPS REBUILD WEAKENED TOOTH
ENAMEL & REVERSE EARLY TOOTH DECAY
Protects Against Cavities
Freshens Breath
Non Burning, Alcohol Free
Gentle pH Balanced
Gentle Mint
32 fl oz (946 mL)

A CLEANER MOUTH
A HEALTHIER YOU®
ClōSYS®
SILVER®
Serious Science for Sensitive Mouths™
How does CloSYS® Silver
with Flouride Work?
CloSYS® Silver Healthy Teeth Mouth Rinse contains fluoride to help protect against cavities. With regular use, it helps rebuild weakened tooth enamel, reverse early tooth decay, and strengthen teeth to improve their appearance. The patented dual action formula contains Cloralstan® which kills bad breath bacteria and neutralizes sulfur mouth odor molecules for long lasting fresh breath. CloSYS® Silver Healthy Teeth Mouth Rinse does not contain alcohol, sulfates, triclosan, and other ingredients that can burn or irritate the mouth so you can rinse longer to get great results!
HEALTHY Mouth = HEALTHY Body
Gentlest.
Oral Care.
Ever.®

A CLEANER MOUTH
A HEALTHIER YOU®
ClōSYS®
SILVER®
Serious Science for Sensitive Mouths™
Our Story
Founder of CloSYS® & Periodontist Dr. Perry Ratcliff had a bold belief that there had to be a better/gentler way to help with oral care. Dr. Ratcliff didn't agree with the common myth ‘If it hurts, it must be good for you’
CloSYS® took a different approach—keep it gentle, yet effective, and people will use it long enough to make a difference in their oral health. After discovering that his first patented formula was not only extremely gentle but incredibly effective, he gathered a small group of dental professionals and business leaders to start their journey toward what is today CloSYS® Oral Care.
What Makes CloSYS®
Product Different?
Simply put, CloSYS® is the Gentlest. Oral Care. Ever.® All CloSYS® formulas are highly effective and extremely gentle so they are not harsh or irritating to sensitive mouths. And because it’s so gentle, it means you can swish it in your mouth longer without having to spit it out early and risk not getting the full benefit of the rinse.
CloSYS® products are free of alcohol, sulfates, triclosan, and other harsh ingredients that can burn or irritate sensitive mouths.

Distributed by:
Rowpar Pharmaceuticals, Inc.
Bridgewater, NJ 08807
1 (800) 643-3337 closys.com
This bottle is recyclable. Please
support recycling in your community
55032-42